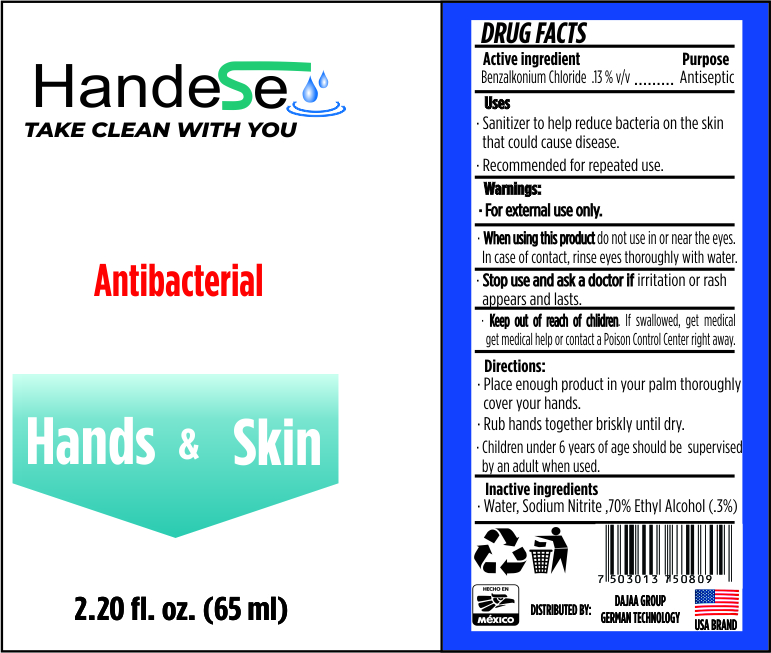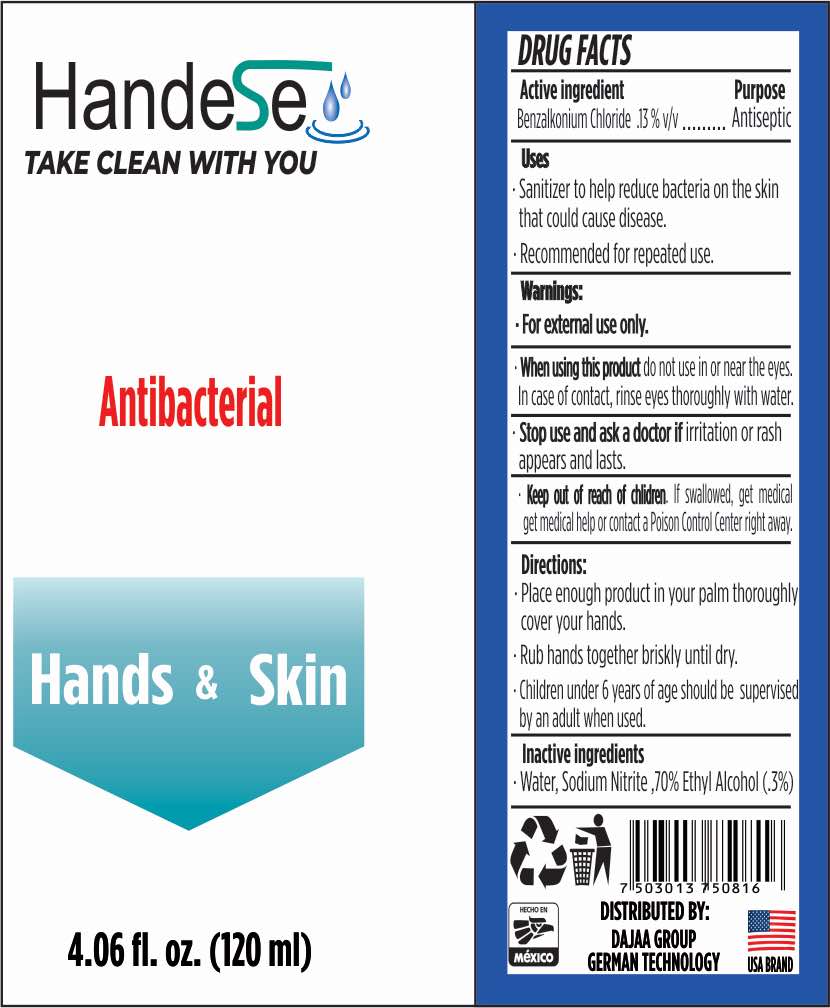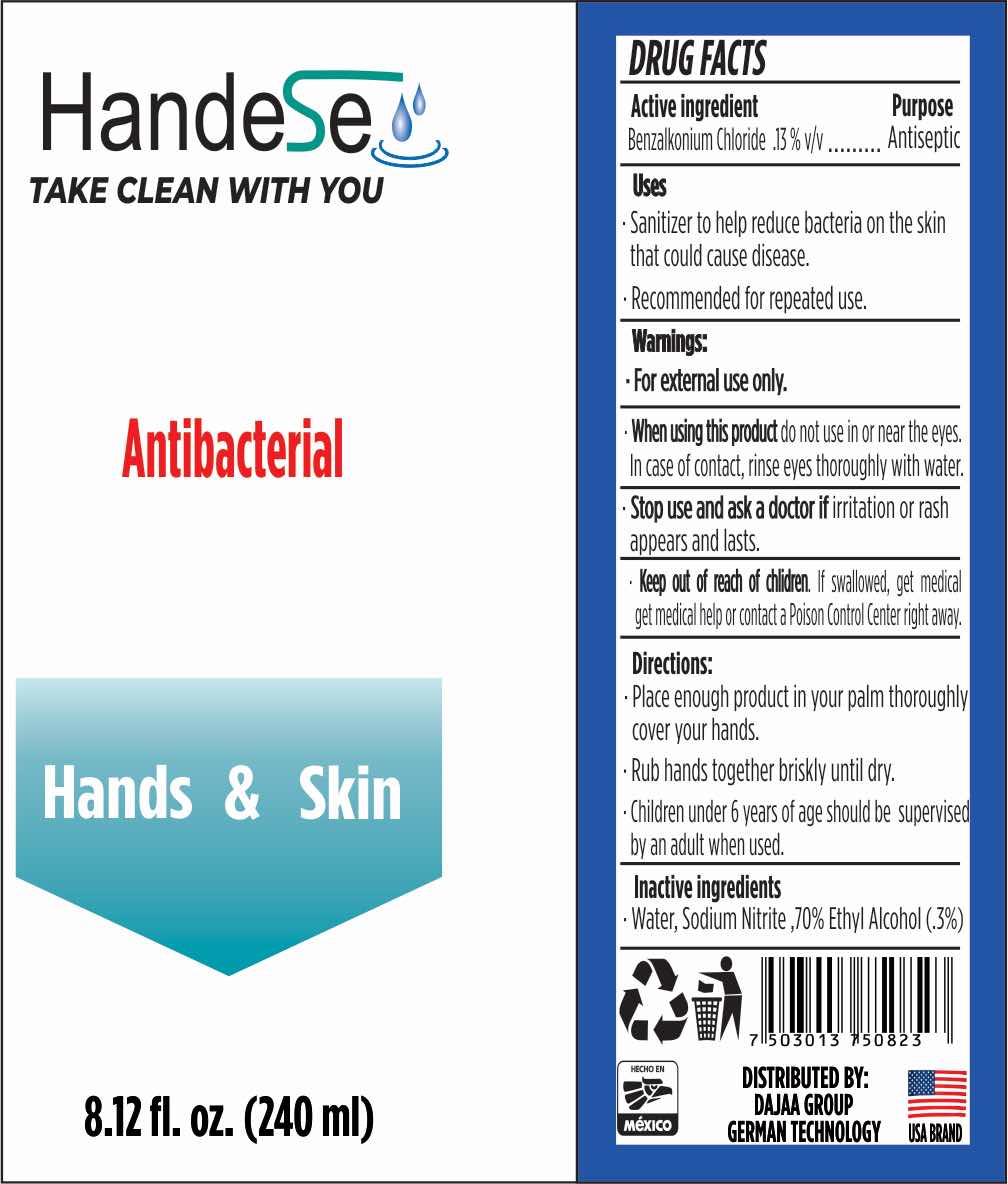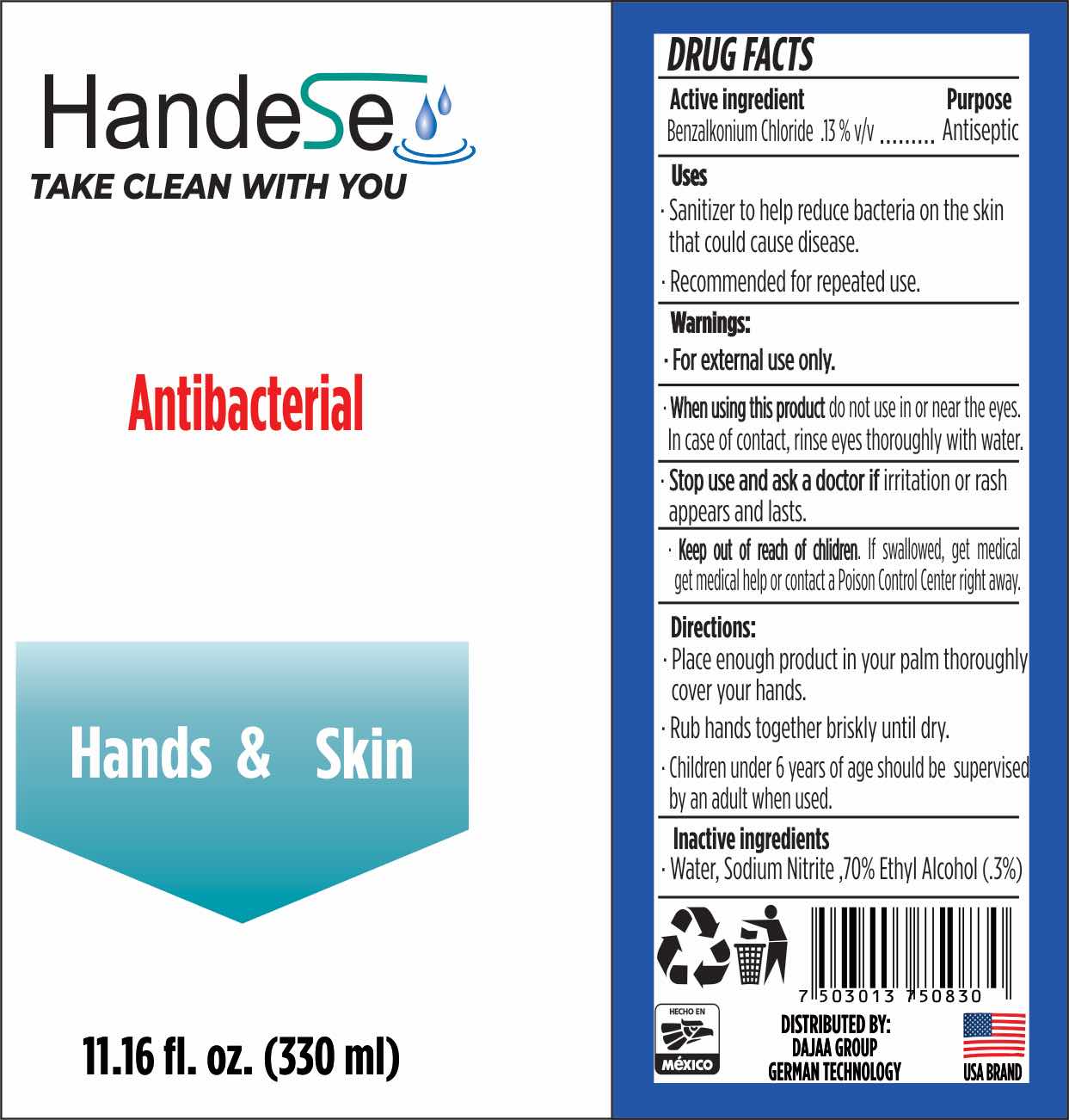 DRUG LABEL: Daranjo
NDC: 78084-003 | Form: SOLUTION
Manufacturer: Matilde Gómez López
Category: otc | Type: HUMAN OTC DRUG LABEL
Date: 20200907

ACTIVE INGREDIENTS: BENZALKONIUM CHLORIDE 1.3 g/1000 mL
INACTIVE INGREDIENTS: SODIUM NITRITE 0.3 g/1000 mL; ALCOHOL 4 mL/1000 mL; WATER

Active Ingredient(s)

Alcohol 70% v/v. Purpose: Antiseptic

Purpose

Antiseptic, Hand Sanitizer

Use

Hand Sanitizer to help reduce bacteria that potentially can cause disease. For use when soap and water are not available.

Warnings

For external use only. Flammable. Keep away from heat or flame

Do not use

- in children less than 2 months of age
- on open skin wounds

When using this product keep out of eyes, ears, and mouth. In case of contact with eyes, rinse eyes thoroughly with water.
Stop use and ask a doctor if irritation or rash occurs. These may be signs of a serious condition.
Keep out of reach of children. If swallowed, get medical help or contact a Poison Control Center right away.

Stop use and ask a doctor if irritation or rash occurs. These may be signs of a serious condition.

Keep out of reach of children. If swallowed, get medical help or contact a Poison Control Center right away.

Directions

- Place enough product on hands to cover all surfaces. Rub hands together until dry.
- Supervise children under 6 years of age when using this product to avoid swallowing.

Other information

- Store between 15-30C (59-86F)
- Avoid freezing and excessive heat above 40C (104F)

Inactive ingredients

purified water USP, alcohol, sodium nitrite.

Package Label - Principal Display Panel

65 mL NDC:78084-003-01

120 mL NDC: 78084-003-02

240 mL NDC: 78084-003-03

330 mL NDC: 78084-003-04